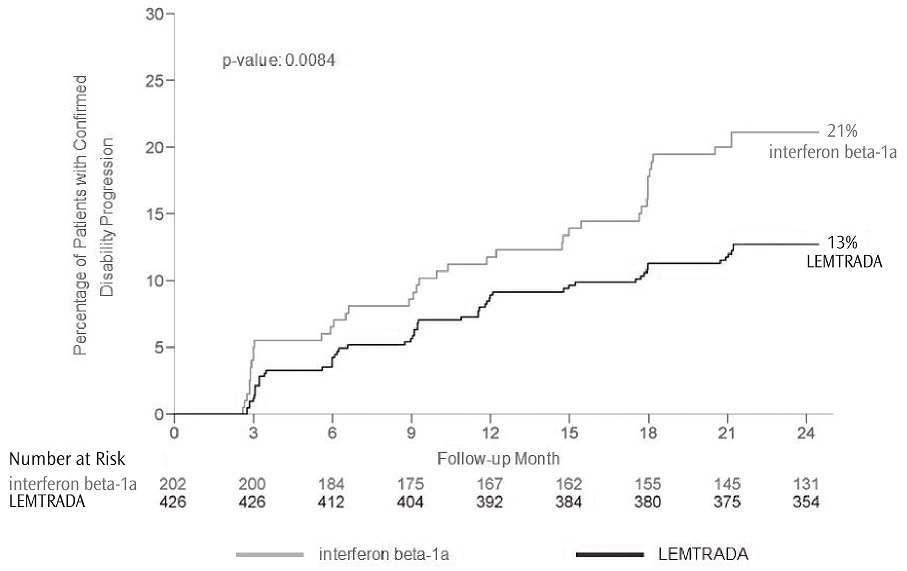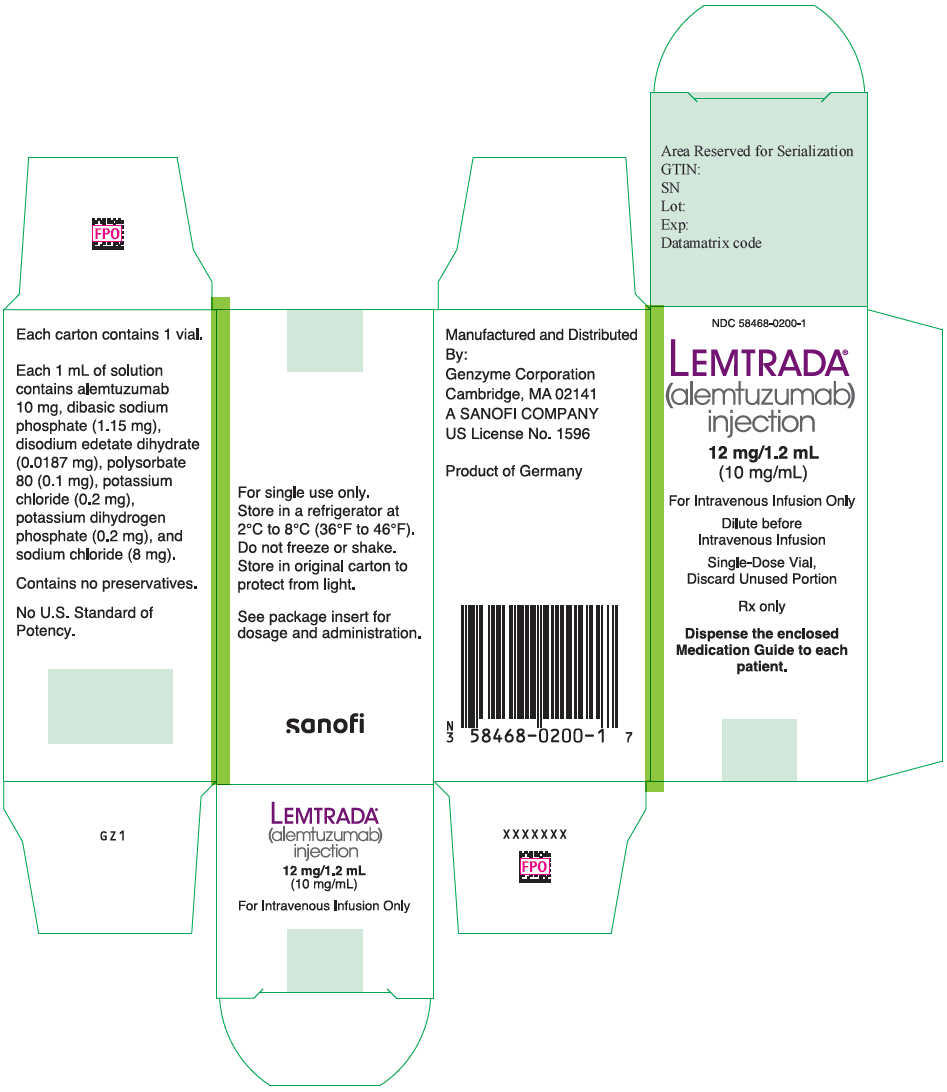 DRUG LABEL: LEMTRADA
NDC: 58468-0200 | Form: INJECTION, SOLUTION, CONCENTRATE
Manufacturer: Genzyme Corporation
Category: prescription | Type: HUMAN PRESCRIPTION DRUG LABEL
Date: 20251103

ACTIVE INGREDIENTS: ALEMTUZUMAB 12 mg/1.2 mL
INACTIVE INGREDIENTS: EDETATE DISODIUM 0.0224 mg/1.2 mL; POTASSIUM CHLORIDE 0.24 mg/1.2 mL; MONOBASIC POTASSIUM PHOSPHATE 0.24 mg/1.2 mL; SODIUM CHLORIDE 9.6 mg/1.2 mL; SODIUM PHOSPHATE, DIBASIC, UNSPECIFIED FORM 1.38 mg/1.2 mL; POLYSORBATE 80 0.12 mg/1.2 mL; WATER

HIGHLIGHTS OF PRESCRIBING INFORMATION

These highlights do not include all the information needed to use LEMTRADA safely and effectively. See full prescribing information for LEMTRADA.
LEMTRADA® (alemtuzumab) injection, for intravenous use
Initial U.S. Approval: 2001

WARNING: AUTOIMMUNITY, INFUSION REACTIONS, STROKE, AND MALIGNANCIES

See full prescribing information for complete boxed warning.

- LEMTRADA causes serious, sometimes fatal, autoimmune conditions such as immune thrombocytopenia and anti-glomerular basement membrane disease. Monitor complete blood counts with differential, serum creatinine levels, and urinalysis with urine cell counts monthly until 48 months after the last dose. (5.1)
- LEMTRADA causes serious and life-threatening infusion reactions. LEMTRADA must be administered in a setting with appropriate equipment and personnel to manage anaphylaxis or serious infusion reactions. Monitor patients for two hours after each infusion. Make patients aware that serious infusion reactions can also occur after the 2-hour monitoring period. (5.2)
- Serious and life-threatening stroke has been reported within 3 days of LEMTRADA administration. Instruct patients to seek immediate medical attention if symptoms of stroke occur. (5.3)
- LEMTRADA may cause an increased risk of malignancies, including thyroid cancer, melanoma, and lymphoproliferative disorders. Perform baseline and yearly skin exams. (5.4)
- LEMTRADA is available only through a restricted distribution program. (5.5)

RECENT MAJOR CHANGES

Warnings and Precautions (5.1, 5.16) | x/202x

1 INDICATIONS AND USAGE

- LEMTRADA is a CD52-directed cytolytic monoclonal antibody indicated for the treatment of relapsing forms of multiple sclerosis (MS), to include relapsing-remitting disease and active secondary progressive disease, in adults. Because of its safety profile, the use of LEMTRADA should generally be reserved for patients who have had an inadequate response to two or more drugs indicated for the treatment of MS. (1.5)
  Limitations of Use:
  LEMTRADA is not recommended for use in patients with clinically isolated syndrome (CIS) because of its safety profile. (1.5)

2 DOSAGE AND ADMINISTRATION

- Baseline laboratory tests are required prior to treatment. (2.1)
- Administer LEMTRADA by intravenous infusion over 4 hours for 2 or more treatment courses:
  Initial treatment of 2 courses:
  - First course: 12 mg/day on 5 consecutive days. (2.3)
  - Second course: 12 mg/day on 3 consecutive days 12 months after first treatment course. (2.3)
  Subsequent treatment courses of 12 mg per day on 3 consecutive days (36 mg total dose) may be administered, as needed, at least 12 months after the last dose of any prior treatment course. (2.3)
- Premedicate with corticosteroids prior to LEMTRADA infusion for the first 3 days of each treatment course. (2.2)
- Administer antiviral agents for herpetic prophylaxis starting on the first day of LEMTRADA dosing and continuing for a minimum of two months after completion of LEMTRADA dosing or until CD4+ lymphocyte count is more than 200 cells per microliter, whichever occurs later. (2.2)
- Must be diluted prior to administration. (2.4)

3 DOSAGE FORMS AND STRENGTHS

Injection: 12 mg/1.2 mL (10 mg/mL) in a single-dose vial. (3)

4 CONTRAINDICATIONS

- Known hypersensitivity or anaphylactic reactions to alemtuzumab or any of the excipients in LEMTRADA (4)
- Infection with Human Immunodeficiency Virus (4)
- Active infection (4)

5 WARNINGS AND PRECAUTIONS

- Immune Thrombocytopenia: Obtain complete blood counts (CBCs) with differential prior to initiation of treatment and at monthly intervals thereafter until 48 months after the last infusion. (5.6)
- Glomerular Nephropathies: Obtain serum creatinine levels, urinalysis with cell counts and urine protein to creatinine ratio prior to initiation of treatment. Monitor serum creatinine levels and urinalysis with cell counts at monthly intervals thereafter until 48 months after the last infusion. (5.7)
- Thyroid Disorders: Obtain thyroid function tests prior to initiation of treatment and every 3 months until 48 months after the last infusion. (5.8)
- Other Autoimmune Cytopenias: Monitor CBCs monthly until 48 months after the last infusion. (2.6, 5.9)
- Autoimmune Hepatitis: If signs of hepatic dysfunction occur, promptly measure serum transaminases and total bilirubin and interrupt or discontinue treatment. (5.10)
- Hemophagocytic Lymphohistiocytosis: Consider this diagnosis and evaluate patients immediately if they develop signs or symptoms of systemic inflammation. Discontinue LEMTRADA if an alternative etiology is not established. (5.11)
- Adult Onset Still's Disease (AOSD): If a patient develops AOSD, they require prompt evaluation and treatment. (5.12)
- Thrombotic Thrombocytopenic Purpura (TTP): Evaluate patients immediately if they develop clinical symptoms or laboratory findings consistent with TTP. Discontinue LEMTRADA if TTP is confirmed or if an alternative etiology is not established. (5.13)
- Autoimmune Encephalitis (AIE): Evaluate patients if they develop signs and symptoms suggestive of AIE, such as subacute onset of memory impairment, altered mental status, psychiatric symptoms, neurological findings, and seizures. (5.14)
- Acquired Hemophilia A: Obtain a coagulopathy panel including aPTT in patients who present with signs such as spontaneous subcutaneous hematomas, extensive bruising, hematuria, epistaxis, or gastrointestinal or other types of bleeding. (5.15)
- Immune-Mediated Colitis: Immune-mediated colitis has been reported in the postmarketing setting. Monitor patients for new or persistent diarrhea or other gastrointestinal symptoms, and evaluate promptly if colitis is suspected. (5.16)
- Infections: Administration is contraindicated in patients with active infection. Do not administer live viral vaccines following a course of LEMTRADA. (4, 5.17)
- Progressive Multifocal Leukoencephalopathy (PML): Withhold LEMTRADA at the first sign or symptom suggestive of PML. (5.18)

6 ADVERSE REACTIONS

Most common adverse reactions (incidence ≥10% and > interferon beta-1a): rash, headache, pyrexia, nasopharyngitis, nausea, urinary tract infection, fatigue, insomnia, upper respiratory tract infection, herpes viral infection, urticaria, pruritus, thyroid gland disorders, fungal infection, arthralgia, pain in extremity, back pain, diarrhea, sinusitis, oropharyngeal pain, paresthesia, dizziness, abdominal pain, flushing, and vomiting. (6.1)

To report SUSPECTED ADVERSE REACTIONS, contact Genzyme Corporation at 1-800-745-4447, option 2 or FDA at 1-800-FDA-1088 or www.fda.gov/medwatch.

8 USE IN SPECIFIC POPULATIONS

Pregnancy: May cause fetal harm. (8.1)

Women of childbearing potential should use effective contraception during and for 4 months after a course of treatment with LEMTRADA. (8.3)

FULL PRESCRIBING INFORMATION

WARNING: AUTOIMMUNITY, INFUSION REACTIONS, STROKE, AND MALIGNANCIES

- LEMTRADA causes serious, sometimes fatal, autoimmune conditions such as immune thrombocytopenia and anti-glomerular basement membrane disease. Monitor complete blood counts with differential, serum creatinine levels, and urinalysis with urine cell counts before starting treatment and then at monthly intervals until 48 months after the last dose of LEMTRADA [see Warnings and Precautions (5.1)].
- LEMTRADA causes serious and life-threatening infusion reactions. LEMTRADA must be administered in a setting with appropriate equipment and personnel to manage anaphylaxis or serious infusion reactions. Monitor patients for two hours after each infusion. Make patients aware that serious infusion reactions can also occur after the 2-hour monitoring period [see Warnings and Precautions (5.2)].
- Serious and life-threatening stroke (including ischemic and hemorrhagic stroke) has been reported within 3 days of LEMTRADA administration. Instruct patients to seek immediate medical attention if symptoms of stroke occur [see Warnings and Precautions (5.3)].
- LEMTRADA may cause an increased risk of malignancies, including thyroid cancer, melanoma, and lymphoproliferative disorders. Perform baseline and yearly skin exams [see Warnings and Precautions (5.4)].
- Because of the risk of autoimmunity, infusion reactions, and malignancies, LEMTRADA is available only through restricted distribution under a Risk Evaluation Mitigation Strategy (REMS) Program. Call 1-855-676-6326 to enroll in the LEMTRADA REMS program [see Warnings and Precautions (5.5)].

1 INDICATIONS AND USAGE

LEMTRADA is indicated for the treatment of relapsing forms of multiple sclerosis (MS), to include relapsing-remitting disease and active secondary progressive disease, in adults. Because of its safety profile, the use of LEMTRADA should generally be reserved for patients who have had an inadequate response to two or more drugs indicated for the treatment of MS [see Warnings and Precautions (5)].

Limitations of Use

LEMTRADA is not recommended for use in patients with clinically isolated syndrome (CIS) because of its safety profile [see Warnings and Precautions (5)].

2 DOSAGE AND ADMINISTRATION

2.1 Testing and Procedures Prior to Treatment

Baseline laboratory tests are required prior to treatment with LEMTRADA [see Dosage and Administration (2.6)]. In addition, prior to starting treatment with LEMTRADA [see Warnings and Precautions (5.15)]:

- complete any necessary immunizations at least 6 weeks prior to treatment.
- determine whether patients have a history of varicella or have been vaccinated for varicella zoster virus (VZV). If not, test the patient for antibodies to VZV and consider vaccination for those who are antibody-negative. Postpone treatment with LEMTRADA until 6 weeks after VZV vaccination.
- perform tuberculosis screening according to local guidelines.
- instruct patients to avoid potential sources of Listeria monocytogenes.

2.2 Recommended Premedication and Concomitant Medication

Corticosteroids

Premedicate patients with high dose corticosteroids (1,000 mg methylprednisolone or equivalent) immediately prior to LEMTRADA infusion and for the first 3 days of each treatment course [see Warnings and Precautions (5.2)].

Herpes Prophylaxis

Administer antiviral prophylaxis for herpetic viral infections starting on the first day of each treatment course and continue for a minimum of two months following treatment with LEMTRADA or until the CD4+ lymphocyte count is at least 200 cells per microliter, whichever occurs later [see Warnings and Precautions (5.15)].

2.3 Recommended Dosage

- The recommended dosage of LEMTRADA is 12 mg/day administered by intravenous infusion for 2 treatment courses: First Treatment Course: 12 mg/day on 5 consecutive days (60 mg total dose).
- Second Treatment Course: 12 mg/day on 3 consecutive days (36 mg total dose) administered 12 months after the first treatment course.

Following the second treatment course, subsequent treatment courses of 12 mg per day on 3 consecutive days (36 mg total dose) may be administered, as needed, at least 12 months after the last dose of any prior treatment courses.

2.4 Preparation Instructions

Follow the steps below to prepare the diluted solution of LEMTRADA for intravenous infusion:

- Inspect LEMTRADA visually for particulate matter and discoloration prior to administration. Do not use if particulate matter is present or the solution is discolored. Do not freeze or shake vials prior to use.
- Withdraw 1.2 mL of LEMTRADA from the vial into a syringe using aseptic technique and inject into a 100 mL bag of sterile 0.9% Sodium Chloride, USP or 5% Dextrose in Water, USP.
- Gently invert the bag to mix the solution. Ensure the sterility of the prepared solution because it contains no antimicrobial preservatives. Each vial is for single use only.

Prior to administration, protect diluted LEMTRADA solution from light and store for as long as 8 hours either at room temperature 15°C to 25°C (59°F to 77°F) or keep refrigerated at conditions 2°C to 8°C (36°F to 46°F).

2.5 Infusion Instructions

Infuse LEMTRADA over 4 hours starting within 8 hours after dilution. Extend the duration of the infusion if clinically indicated.

Administer LEMTRADA in a setting in which equipment and personnel to appropriately manage anaphylaxis, serious infusion reactions, myocardial ischemia, myocardial infarction, and cerebrovascular and respiratory adverse reactions are available [see Warnings and Precautions (5.2)].

Do not add or simultaneously infuse other drug substances through the same intravenous line. Do not administer as an intravenous push or bolus.

Obtain a baseline ECG. Monitor vital signs before the infusion and periodically during the infusion. Provide appropriate symptomatic treatment for infusion reactions as needed. Consider immediate discontinuation of the intravenous infusion if severe infusion reactions occur.

Observe patients for infusion reactions during and for at least 2 hours after each LEMTRADA infusion. Consider longer periods of observation if clinically indicated. Inform patients that they should report symptoms that occur during and after each infusion because they may indicate a need for prompt medical intervention [see Warnings and Precautions (5.2)].

2.6 Laboratory Testing and Monitoring to Assess Safety

Measure the urine protein to creatinine ratio prior to initiation of treatment. Conduct the following laboratory tests at baseline and at periodic intervals until 48 months after the last treatment course of LEMTRADA in order to monitor for early signs of potentially serious adverse effects:

- Complete blood count (CBC) with differential (prior to treatment initiation and at monthly intervals thereafter)
- Serum creatinine levels (prior to treatment initiation and at monthly intervals thereafter)
- Urinalysis with urine cell counts (prior to treatment initiation and at monthly intervals thereafter)
- A test of thyroid function, such as thyroid stimulating hormone (TSH) level (prior to treatment initiation and every 3 months thereafter)
- Serum transaminases (alanine aminotransferase [ALT] and aspartate aminotransferase [AST]) and total bilirubin levels (prior to treatment initiation and periodically thereafter)

Conduct baseline and yearly skin exams to monitor for melanoma [see Warnings and Precautions (5.4)].

3 DOSAGE FORMS AND STRENGTHS

Injection: 12 mg/1.2 mL (10 mg/mL) in a single-dose vial. LEMTRADA is a clear and colorless to slightly yellow solution that requires dilution prior to intravenous infusion.

4 CONTRAINDICATIONS

LEMTRADA is contraindicated in patients:

- with known hypersensitivity or anaphylactic reactions to alemtuzumab or any of the excipients in LEMTRADA
- who are infected with human immunodeficiency virus (HIV) because LEMTRADA causes prolonged reductions of CD4+ lymphocyte counts
- with active infection

5 WARNINGS AND PRECAUTIONS

5.1 Autoimmunity

Treatment with LEMTRADA can result in the formation of autoantibodies and increase the risk of serious autoimmune conditions, which may be life threatening.

In clinical studies (controlled and open-label extension), the following serious autoimmune conditions were reported in LEMTRADA-treated patients, which are described in separate warnings:

- thyroid disorders (36.8%) [see Warnings and Precautions (5.8)]
- immune thrombocytopenia (2%) [see Warnings and Precautions (5.6)]
- glomerular nephropathies (0.3%) [see Warnings and Precautions 5.7]
- autoimmune hemolytic anemia (0.3%), autoimmune pancytopenia (0.2%), and autoimmune neutropenia (0.1%) [see Warnings and Precautions (5.9)]
- acquired hemophilia A (anti-Factor VIII antibodies) (0.1%) [see Warnings and Precautions (5.15)]

In clinical studies (controlled and open-label extension), vitiligo (0.3%), undifferentiated connective tissue disorders (0.2%), type 1 diabetes (0.2%), rheumatoid arthritis (0.1%), and retinal pigment epitheliopathy (0.1%) were also reported in LEMTRADA-treated patients.

In the postmarketing setting, cases of autoimmune hepatitis [see Warnings and Precautions (5.10)], hemophagocytic lymphohistiocytosis [see Warnings and Precautions (5.11)], Adult Onset Still's Disease [see Warnings and Precautions (5.12)], thrombotic thrombocytopenic purpura [see Warnings and Precautions (5.13)], autoimmune encephalitis [see Warnings and Precautions (5.14)], immune-mediated colitis [see Warnings and Precautions (5.16)], Guillain-Barré syndrome, and vasculitis have been reported.

Chronic inflammatory demyelinating polyradiculoneuropathy has been reported in the treatment of patients with B-cell chronic lymphocytic leukemia (B-CLL), as well as other autoimmune disorders, generally at higher and more frequent doses than recommended in MS.

Autoantibodies may be transferred from the mother to the fetus during pregnancy. A case of transplacental transfer of anti-thyrotropin receptor antibodies resulting in neonatal Graves' disease occurred after alemtuzumab treatment in the mother [see Use in Specific Populations (8.1)].

LEMTRADA may increase the risk of other autoimmune conditions because of the broad range of autoantibody formation with LEMTRADA.

Measure the urine protein to creatinine ratio prior to initiation of treatment. Monitor complete blood counts with differential, serum creatinine levels, and urinalysis with urine cell counts before starting treatment and then at monthly intervals until 48 months after the last dose of LEMTRADA to allow for early detection and treatment of autoimmune adverse reactions [see Dosage and Administration (2.6)]. After 48 months, testing should be performed based on clinical findings suggestive of autoimmunity.

LEMTRADA is available only through a restricted program under a REMS [see Warnings and Precautions (5.5)].

5.2 Infusion Reactions

LEMTRADA causes cytokine release syndrome resulting in infusion reactions, some of which may be serious and life threatening. In clinical studies, 92% of LEMTRADA-treated patients experienced infusion reactions. In some patients, infusion reactions were reported more than 24 hours after LEMTRADA infusion. Serious reactions occurred in 3% of patients and included anaphylaxis in 2 patients (including anaphylactic shock), angioedema, bronchospasm, hypotension, chest pain, bradycardia, tachycardia (including atrial fibrillation), transient neurologic symptoms, hypertension, headache, pyrexia, and rash. Other infusion reactions included nausea, urticaria, pruritus, insomnia, chills, flushing, fatigue, dyspnea, pulmonary infiltrates, dysgeusia, dyspepsia, dizziness, and pain. In clinical studies, 0.6% of patients with infusion reactions received epinephrine or atropine.

During postmarketing use, cases of pulmonary alveolar hemorrhage, myocardial ischemia, myocardial infarction, stroke (including ischemic and hemorrhagic stroke), and cervicocephalic (e.g., vertebral, carotid) arterial dissection have been reported. Reactions may occur following any of the doses during the treatment course. In the majority of cases, time to onset was within 1 to 3 days of LEMTRADA infusion. Patients should be informed about the signs and symptoms and advised to seek immediate medical attention if any of these symptoms occur. Cases of severe (including fatal) neutropenia have been reported within 2 months of LEMTRADA infusion; some cases resolved with receiving granulocyte-colony stimulating factor treatment. Mild to moderate decreases in platelet counts, starting at the time of alemtuzumab infusion and often resolving without treatment, have been reported. Other serious and sometimes fatal infusion reactions (e.g., hypoxia, syncope, acute respiratory distress syndrome, respiratory arrest, myocardial infarction, acute cardiac insufficiency, cardiac arrest) have been reported in the treatment of patients with B-CLL, as well as other disorders, generally at higher and more frequent doses than recommended in MS.

Premedicate patients with corticosteroids immediately prior to LEMTRADA infusion for the first 3 days of each treatment course. In clinical studies, patients received 1,000 mg of methylprednisolone for the first 3 days of each LEMTRADA treatment course. Consider pretreatment with antihistamines and/or antipyretics prior to LEMTRADA administration. Infusion reactions may occur despite pretreatment.

Consider additional monitoring in patients with medical conditions which predispose them to cardiovascular or pulmonary compromise. Physicians should alert patients that an infusion reaction could occur within 48 hours of infusion.

LEMTRADA can only be administered in certified healthcare settings that have on-site access to equipment and personnel trained to manage infusion reactions (including anaphylaxis, cerebrovascular, cardiac and respiratory emergencies) [see Dosage and Administration (2.5)].

LEMTRADA is available only through a restricted program under a REMS [see Warnings and Precautions (5.5)].

5.3 Stroke and Cervicocephalic Arterial Dissection

Stroke

In the postmarketing setting, serious and life-threatening stroke (including ischemic and hemorrhagic stroke) has been reported within 3 days of LEMTRADA administration, with most cases occurring within 1 day.

Cervicocephalic Arterial Dissection

In the postmarketing setting, cases of cervicocephalic (e.g., vertebral, carotid) arterial dissection involving multiple arteries have been reported within 3 days of LEMTRADA administration. Ischemic stroke was reported in one of these cases.

Educate patients on the symptoms of stroke and cervicocephalic (e.g., carotid, vertebral) arterial dissection. Instruct patients to seek immediate medical attention if symptoms of stroke or cervicocephalic arterial dissection occur.

5.4 Malignancies

Thyroid Cancer

LEMTRADA may increase the risk of thyroid cancer. In controlled clinical studies, 3 of 919 (0.3%) LEMTRADA-treated patients developed thyroid cancer, compared to none in the interferon beta-1a–treated group. However, screening for thyroid cancer was performed more frequently in the LEMTRADA-treated group, because of the higher incidence of autoimmune thyroid disorders in those patients. Two additional cases of thyroid cancer in LEMTRADA-treated patients occurred in uncontrolled studies.

Patients and healthcare providers should monitor for symptoms of thyroid cancer including a new lump or swelling in the neck, pain in the front of the neck, persistent hoarseness or other voice changes, trouble swallowing or breathing, or a constant cough not due to an upper respiratory tract infection.

Melanoma

LEMTRADA may increase the risk of melanoma. In MS clinical studies (controlled and open-label extension), 5 of 1486 (0.3%) LEMTRADA-treated patients developed melanoma or melanoma in situ. One of those patients had evidence of locally advanced disease.

Perform baseline and yearly skin examinations to monitor for melanoma in patients receiving LEMTRADA.

Lymphoproliferative Disorders and Lymphoma

Cases of lymphoproliferative disorders and lymphoma have occurred in LEMTRADA-treated patients with MS, including a MALT lymphoma, Castleman's Disease, and a fatality following treatment of non-Epstein Barr Virus–associated Burkitt's lymphoma. There are postmarketing reports of Epstein Barr Virus–associated lymphoproliferative disorders in non-MS patients.

Because LEMTRADA is an immunomodulatory therapy, caution should also be exercised in initiating LEMTRADA in patients with preexisting or ongoing malignancies.

LEMTRADA is available only through a restricted program under a REMS [see Warnings and Precautions (5.5)].

5.5 LEMTRADA REMS Program

LEMTRADA is available only through a restricted program under a REMS called the LEMTRADA REMS Program because of the risks of autoimmunity, infusion reactions, and malignancies [see Warnings and Precautions (5.1, 5.2, 5.4)].

Notable requirements of the LEMTRADA REMS Program include the following:

- Prescribers must be certified with the program by enrolling and completing training.
- Patients must enroll in the program and comply with ongoing monitoring requirements [see Dosage and Administration (2.6)].
- Pharmacies must be certified with the program and must only dispense to certified healthcare facilities that are authorized to receive LEMTRADA.
- Healthcare facilities must enroll in the program and verify that patients are authorized before infusing LEMTRADA. Healthcare facilities must have on-site access to equipment and personnel trained to manage infusion reactions.

Further information, including a list of qualified healthcare facilities, is available at 1-855-676-6326.

5.6 Immune Thrombocytopenia

Immune thrombocytopenia (ITP) occurred in 2% of LEMTRADA-treated patients in MS clinical studies (controlled and open-label extension).

In a controlled clinical study in patients with MS, one LEMTRADA-treated patient developed ITP that went unrecognized prior to the implementation of monthly blood monitoring requirements, and died from intracerebral hemorrhage. Nadir platelet counts ≤20,000 cells per microliter as a result of ITP occurred in 2% of all LEMTRADA-treated patients in clinical studies in MS. Anti-platelet antibodies did not precede ITP onset. ITP has been diagnosed more than 3 years after the last LEMTRADA dose.

Symptoms of ITP include easy bruising, petechiae, spontaneous mucocutaneous bleeding (e.g., epistaxis, hemoptysis), and heavier than normal or irregular menstrual bleeding. Hemoptysis may also be indicative of anti-glomerular basement membrane (GBM) disease [see Warnings and Precautions (5.7)], and an appropriate differential diagnosis has to be undertaken. Remind the patient to remain vigilant for symptoms they may experience and to seek immediate medical help if they have any concerns.

Obtain complete blood counts (CBCs) with differential prior to initiation of treatment and at monthly intervals thereafter until 48 months after the last infusion [see Dosage and Administration (2.6)]. After this period of time, testing should be performed based on clinical findings suggestive of ITP. If ITP is suspected, a complete blood count should be obtained immediately. If ITP onset is confirmed, promptly initiate appropriate medical intervention.

5.7 Glomerular Nephropathies Including Anti-glomerular Basement Membrane Disease

Glomerular nephropathies occurred in 0.3% of LEMTRADA-treated patients in MS clinical studies. There were 3 cases of membranous glomerulonephritis and 2 cases of anti-glomerular basement membrane (anti-GBM) disease.

In postmarketing cases, some LEMTRADA-treated patients with anti-GBM disease developed end-stage renal disease requiring dialysis or renal transplantation. Urgent evaluation and treatment are required because early treatment can improve the preservation of renal function. Anti-GBM disease can be life-threatening if left untreated. Alveolar hemorrhage, manifested as hemoptysis, is a common component of anti-GBM disease and has been reported in postmarketing cases. Cases of anti-GBM disease have been diagnosed up to 40 months after the last dose of LEMTRADA.

Symptoms of nephropathy may include edema, hematuria, change in urine color, decreased urine output, fatigue, dyspnea, and hemoptysis. Patients and caregivers should be instructed to seek medical advice if they have concerns.

Obtain serum creatinine levels, urinalysis with cell counts, and urine protein to creatinine ratio prior to initiation of treatment. Obtain serum creatinine levels and urinalysis with cell counts at monthly intervals thereafter until 48 months after the last infusion. After this period of time, testing should be performed based on clinical findings suggestive of nephropathies.

For urine dipstick results of 1+ protein or greater, measure the urine protein to creatinine ratio. For urine protein to creatinine ratio greater than 200 mg/g, increase in serum creatinine greater than 30%, or unexplained hematuria, perform further evaluation for nephropathies. Increased serum creatinine with hematuria or signs of pulmonary involvement of anti-GBM disease (e.g., hemoptysis, exertional dyspnea) warrant immediate evaluation. Early detection and treatment of nephropathies may decrease the risk of poor outcomes.

5.8 Thyroid Disorders

Thyroid endocrine disorders, including autoimmune thyroid disorders, occurred in 36.8% of LEMTRADA-treated patients in MS clinical studies (controlled and open-label extension). Newly diagnosed thyroid disorders occurred throughout the uncontrolled clinical study follow-up period, more than 7 years after the first LEMTRADA dose. Autoimmune thyroid disorders included Graves' disease, hyperthyroidism, hypothyroidism, autoimmune thyroiditis, and goiter. Graves' ophthalmopathy with decreased vision, eye pain, and exophthalmos occurred in 2% of LEMTRADA-treated patients. Seven patients required surgical orbital decompression. Serious thyroid events occurred in about 5.2% of LEMTRADA-treated patients in clinical studies and included cardiac and psychiatric events associated with thyroid disease. Of all LEMTRADA-treated patients, 3.8% underwent thyroidectomy.

Thyroid disease poses special risks in women who are pregnant [see Use in Specific Populations (8.1)].

Obtain thyroid function tests, such as TSH levels, prior to initiation of treatment and every 3 months thereafter until 48 months after the last infusion. Continue to test thyroid function after 48 months if clinically indicated or in case of pregnancy.

In patients with ongoing thyroid disorder, LEMTRADA should be administered only if the potential benefit justifies the potential risks.

5.9 Other Autoimmune Cytopenias

Autoimmune cytopenias such as neutropenia (0.1%), hemolytic anemia (0.3%), and pancytopenia (0.2%) occurred in LEMTRADA-treated patients in MS clinical studies (controlled and open-label extension). In cases of autoimmune hemolytic anemia, patients tested positive for direct antiglobulin antibodies, and nadir hemoglobin levels ranged from 2.9–8.6 g/dL. Symptoms of autoimmune hemolytic anemia include weakness, chest pain, jaundice, dark urine, and tachycardia. One LEMTRADA-treated patient with autoimmune pancytopenia died from sepsis.

During postmarketing use, additional autoimmune cytopenias, including fatal autoimmune hemolytic anemia and aplastic anemia, have been reported in the treatment of patients with B-CLL, as well as other disorders, generally at higher and more frequent doses of alemtuzumab than recommended in MS.

Use CBC results to monitor for cytopenias. Prompt medical intervention is indicated if a cytopenia is confirmed.

5.10 Autoimmune Hepatitis

Autoimmune hepatitis causing clinically significant liver injury, including acute liver failure requiring transplant, has been reported in patients treated with LEMTRADA in the postmarketing setting. If a patient develops clinical signs, including unexplained liver enzyme elevations or symptoms suggestive of hepatic dysfunction (e.g., unexplained nausea, vomiting, abdominal pain, fatigue, anorexia, or jaundice and/or dark urine), promptly measure serum transaminases and total bilirubin and interrupt or discontinue treatment with LEMTRADA, as appropriate.

Prior to starting treatment with LEMTRADA, obtain serum transaminases (ALT and AST) and total bilirubin levels. Obtain transaminase levels and total bilirubin levels at periodic intervals until 48 months after the last dose.

5.11 Hemophagocytic Lymphohistiocytosis

Hemophagocytic lymphohistiocytosis (HLH) has occurred in patients taking LEMTRADA. HLH is a life-threatening syndrome of pathologic immune activation characterized by clinical signs and symptoms of extreme systemic inflammation. It is associated with high mortality rates if not recognized early and treated. Common findings include fever, hepatosplenomegaly, rash, lymphadenopathy, neurologic symptoms (e.g., mental status changes, ataxia, or seizures), cytopenias, high serum ferritin, hypertriglyceridemia, and liver function and coagulation abnormalities. Hemophagocytosis may be seen on histologic examination of bone marrow, spleen, or lymph nodes. In cases of HLH reported with LEMTRADA, most patients presented with fever, elevated ferritin, transaminitis, hypertriglyceridemia, and all patients required hospitalization. Although the small number of cases limits the ability to draw conclusions pertaining to mean or range of latency for HLH, symptoms have been reported to occur within approximately thirteen months to thirty-three months following the initiation of treatment. Patients who develop early manifestations of pathologic immune activation should be evaluated immediately, and a diagnosis of HLH should be considered. LEMTRADA should be discontinued if an alternate etiology for the signs or symptoms cannot be established.

5.12 Adult Onset Still's Disease (AOSD)

During postmarketing use, Adult Onset Still's Disease (AOSD) has been reported in patients treated with LEMTRADA. AOSD is a rare inflammatory condition that requires urgent evaluation and treatment. Patients with AOSD may have a combination of the following signs and symptoms: fever, arthritis, rash, and leukocytosis in the absence of infections, malignancies, and other rheumatic conditions. Patients with manifestations of AOSD should be evaluated immediately and LEMTRADA should be discontinued if an alternate etiology for the signs or symptoms cannot be established.

5.13 Thrombotic Thrombocytopenic Purpura (TTP)

TTP has been reported in patients treated with LEMTRADA. TTP is characterized by thrombocytopenia, microangiopathic hemolytic anemia, neurological sequelae, fever, and renal impairment. TTP is associated with high morbidity and mortality rates if not recognized and treated early. LEMTRADA should be discontinued if TTP is confirmed or an alternate etiology for the signs or symptoms cannot be established.

5.14 Autoimmune Encephalitis (AIE)

During postmarketing use, cases of AIE have been reported in patients treated with LEMTRADA. AIE can present with a variety of clinical manifestations, including subacute onset of memory impairment, altered mental status, psychiatric symptoms, neurological findings, and seizures. LEMTRADA should be discontinued if AIE is confirmed by the presence of neural autoantibodies or an alternate etiology cannot be established.

5.15 Acquired Hemophilia A

Cases of acquired hemophilia A (anti-Factor VIII antibodies) have been reported in both the clinical trial and postmarketing settings. Patients typically present with spontaneous subcutaneous hematomas and extensive bruising, although hematuria, epistaxis, gastrointestinal, or other types of bleeding may occur. Obtain a coagulopathy panel including aPTT in patients who present with such symptoms. Patients should be informed about the signs and symptoms of acquired hemophilia A and advised to seek immediate medical attention if any of these symptoms occur.

5.16 Immune-Mediated Colitis

Immune-mediated colitis, which can present as a severe and acute-onset form of colitis, has been reported in patients receiving LEMTRADA in the postmarketing setting. Some cases of colitis were serious, requiring hospitalization. Systemic corticosteroids were required in some of these patients. The time from treatment initiation to onset of symptoms in these cases ranged from a few months to years.

Monitor patients for immune-mediated colitis during and after LEMTRADA treatment, and evaluate promptly if signs and symptoms that may indicate immune-mediated colitis, such as new or persistent diarrhea or other gastrointestinal signs and symptoms, occur.

It is unknown whether immune-mediated colitis in patients treated with LEMTRADA is a monophasic disorder, or whether recurrent flares (as are seen in patients with inflammatory bowel disease) will occur.

5.17 Infections

Infections occurred in 71% of LEMTRADA-treated patients compared to 53% of patients treated with interferon beta-1a in controlled clinical studies in MS up to 2 years in duration. Infections that occurred more often in LEMTRADA-treated patients than interferon beta-1a patients included nasopharyngitis, urinary tract infection, upper respiratory tract infection, sinusitis, herpetic infections, influenza, and bronchitis. Serious infections occurred in 3% of patients treated with LEMTRADA as compared to 1% of patients treated with interferon beta-1a. Serious infections in the LEMTRADA group included: appendicitis, gastroenteritis, pneumonia, herpes zoster, and tooth infection.

Do not administer live viral vaccines following a course of LEMTRADA. Patients treated with LEMTRADA have altered immunity and may be at increased risk of infection following administration of live viral vaccines.

LEMTRADA administration is contraindicated in patients with active infection [see Contraindications (4)].

Concomitant use of LEMTRADA with antineoplastic or immunosuppressive therapies could increase the risk of immunosuppression.

Opportunistic Infections

In the postmarketing setting, serious, sometimes fatal, opportunistic infections have been reported in patients taking LEMTRADA, including aspergillosis, coccidioidomycosis, histoplasmosis, Pneumocystis jirovecii pneumonia, nocardiosis, Epstein-Barr virus, and cytomegalovirus infections.

Listeria Monocytogenes Infections

Listeria monocytogenes infections (e.g., meningitis, encephalitis, sepsis, and gastroenteritis), including fatal cases of Listeria meningoencephalitis, have occurred in LEMTRADA-treated patients. Listeria infections have occurred as early as 3 days after treatment and up to 8 months after the last LEMTRADA dose. The duration of increased risk for Listeria infection after LEMTRADA treatment is unknown.

Advise patients to avoid or adequately heat foods that are potential sources of Listeria monocytogenes (e.g., deli meat, dairy products made with unpasteurized milk, soft cheeses, or undercooked meat, seafood, or poultry). Initiate these Listeria precautions prior to starting LEMTRADA treatment. The incubation period for Listeria monocytogenes ranges from 3 to 70 days. In most cases, signs and symptoms of invasive listeriosis start within 1 month of exposure to Listeria monocytogenes. Symptoms of Listeria infection include fever, chills, diarrhea, nausea, vomiting, headache, pains in joints and muscles, neck stiffness, difficulty walking, mental status changes, coma, and other neurologic changes. As is the case with many infections, treatment cannot always prevent mortality and morbidity related to Listeria infections. Therefore, advise patients to watch for symptoms of Listeria infection and seek prompt medical help if symptoms occur.

Herpes Viral Infections

In controlled clinical studies, 16% of LEMTRADA-treated patients developed a herpes viral infection compared to 3% of interferon beta-1a patients. These events included oral herpes (8.8%), herpes zoster (4.2%), herpes simplex (1.8%), and genital herpes (1.3%). Serious herpetic infections in LEMTRADA-treated patients included primary varicella (0.1%), herpes zoster (0.2%), and herpes meningitis (0.1%). Administer antiviral agents for herpetic prophylaxis at appropriate suppressive dosing regimens. Administer antiviral prophylaxis for herpetic viral infections starting on the first day of each treatment course and continue for a minimum of two months following treatment with LEMTRADA or until the CD4+ lymphocyte count is ≥200 cells per microliter, whichever occurs later [see Dosage and Administration (2.2)].

Human Papilloma Virus

Cervical human papilloma virus (HPV) infection, including cervical dysplasia, occurred in 2% of LEMTRADA-treated patients. Annual HPV screening is recommended for female patients.

Tuberculosis

Tuberculosis occurred in patients treated with LEMTRADA and interferon beta-1a in controlled clinical studies. Active and latent tuberculosis cases occurred in 0.3% of LEMTRADA-treated patients, most often in endemic regions. Perform tuberculosis screening according to local guidelines prior to initiation of LEMTRADA. For patients testing positive in tuberculosis screening, treat by standard medical practice prior to therapy with LEMTRADA.

Fungal Infections

Fungal infections, especially oral and vaginal candidiasis, occurred more commonly in LEMTRADA-treated patients (12%) than in patients treated with interferon beta-1a (3%) in controlled clinical studies in MS.

Infections in Non-MS Patients

During postmarketing use, serious and sometimes fatal viral, bacterial, protozoan, and fungal infections, including some due to reactivation of latent infections, have been reported in the treatment of patients with B-CLL, as well as other disorders, generally at higher and more frequent doses than recommended in MS.

Hepatitis

No data are available on the association of LEMTRADA with Hepatitis B virus (HBV) or Hepatitis C virus (HCV) reactivation because patients with evidence of active or chronic infections were excluded from the clinical studies. Consider screening patients at high risk of HBV and/or HCV infection before initiation of LEMTRADA and exercise caution in prescribing LEMTRADA to patients identified as carriers of HBV and/or HCV as these patients may be at risk of irreversible liver damage relative to a potential virus reactivation as a consequence of their pre-existing status.

5.18 Progressive Multifocal Leukoencephalopathy (PML)

Progressive multifocal leukoencephalopathy (PML) has occurred in a patient with MS treated with LEMTRADA. PML is an opportunistic viral infection of the brain caused by the JC virus (JCV) that typically only occurs in patients who are immunocompromised, and that usually leads to death or severe disability. PML was diagnosed two months after the second course of LEMTRADA. The patient had previously received multiple MS therapies, but had not received other drugs for treatment of MS for more than one year. The patient had no other identified systemic medical conditions resulting in compromised immune system function and had not previously been treated with natalizumab, which has a known association with PML. The patient was not taking any immunosuppressive or immunomodulatory medications concomitantly. After the diagnosis of PML, the patient developed immune reconstitution inflammatory syndrome (IRIS). The patient's condition improved, but mild residual neurologic sequelae remained at last follow-up.

At the first sign or symptom suggestive of PML, withhold LEMTRADA and perform an appropriate diagnostic evaluation. Typical symptoms associated with PML are diverse, progress over days to weeks, and include progressive weakness on one side of the body or clumsiness of limbs, disturbance of vision, and changes in thinking, memory, and orientation leading to confusion and personality changes.

MRI findings may be apparent before clinical signs or symptoms. Cases of PML, diagnosed based on MRI findings and the detection of JCV DNA in the cerebrospinal fluid in the absence of clinical signs or symptoms specific to PML, have been reported in patients treated with other MS medications associated with PML. Many of these patients subsequently became symptomatic with PML. Therefore, monitoring with MRI for signs that may be consistent with PML may be useful, and any suspicious findings should lead to further investigation to allow for an early diagnosis of PML, if present. Following discontinuation of another MS medication associated with PML, lower PML-related mortality and morbidity have been reported in patients who were initially asymptomatic at diagnosis compared to patients who had characteristic clinical signs and symptoms at diagnosis. It is not known whether these differences are due to early detection and discontinuation of MS treatment or due to differences in disease in these patients.

5.19 Acute Acalculous Cholecystitis

LEMTRADA may increase the risk of acute acalculous cholecystitis. In controlled clinical studies, 0.2% of LEMTRADA-treated MS patients developed acute acalculous cholecystitis, compared to 0% of patients treated with interferon beta-1a. During postmarketing use, additional cases of acute acalculous cholecystitis have been reported in LEMTRADA-treated patients. Time to onset of symptoms ranged from less than 24 hours to 2 months after LEMTRADA infusion. Typical risk or predisposing factors such as concurrent critical illness was often not reported. Abnormal ultrasound or computed tomography was used to support the diagnosis of acute acalculous cholecystitis in some cases. Some patients were treated conservatively with antibiotics and recovered without surgical intervention, whereas others underwent cholecystectomy.

Symptoms of acute acalculous cholecystitis include abdominal pain, abdominal tenderness, fever, nausea, and vomiting. Leukocytosis and abnormal liver enzymes are also commonly observed. Acute acalculous cholecystitis is a condition that is associated with high morbidity and mortality rates if not diagnosed early and treated. If acute acalculous cholecystitis is suspected, evaluate and treat promptly.

5.20 Pneumonitis

In clinical studies, 6 of 1217 (0.5%) LEMTRADA-treated patients had pneumonitis of varying severity. Cases of hypersensitivity pneumonitis and pneumonitis with fibrosis occurred in clinical studies. Patients should be advised to report symptoms of pneumonitis, which may include shortness of breath, cough, wheezing, chest pain or tightness, and hemoptysis.

5.21 Drug Products with Same Active Ingredient

LEMTRADA contains the same active ingredient (alemtuzumab) found in CAMPATH®. If LEMTRADA is considered for use in a patient who has previously received CAMPATH, exercise increased vigilance for additive and long-lasting effects on the immune system.

6 ADVERSE REACTIONS

The following serious adverse reactions are described below and elsewhere in the labeling:

- Autoimmunity [see Boxed Warning and Warnings and Precautions (5.1)]
- Infusion Reactions [see Boxed Warning and Warnings and Precautions (5.2)]
- Stroke and Cervicocephalic Arterial Dissection [see Warnings and Precautions (5.3)]
- Malignancies [see Warnings and Precautions (5.4)]
- Immune Thrombocytopenia [see Warnings and Precautions (5.6)]
- Glomerular Nephropathies Including Anti-glomerular Basement Membrane Disease [see Warnings and Precautions (5.7)]
- Thyroid Disorders [see Warnings and Precautions (5.8)]
- Other Autoimmune Cytopenias [see Warnings and Precautions (5.9)]
- Autoimmune Hepatitis [see Warnings and Precautions (5.10)]
- Hemophagocytic Lymphohistiocytosis [see Warnings and Precautions (5.11)]
- Adult Onset Still's Disease [see Warnings and Precautions (5.12)]
- Thrombotic Thrombocytopenic Purpura (TTP) [see Warnings and Precautions (5.13)]
- Autoimmune Encephalitis (AIE) [see Warnings and Precautions (5.14)]
- Acquired Hemophilia A [see Warnings and Precautions (5.15)]
- Immune-Mediated Colitis [see Warnings and Precautions (5.16)]
- Infections [see Warnings and Precautions (5.17)]
- Progressive Multifocal Leukoencephalopathy (PML) [see Warnings and Precautions (5.18)]
- Acute Acalculous Cholecystitis [see Warnings and Precautions (5.19)]
- Pneumonitis [see Warnings and Precautions (5.20)]

6.1 Clinical Trials Experience

Because clinical trials are conducted under widely varying conditions, adverse reaction rates observed in the clinical trials of a drug cannot be directly compared to rates in the clinical trials of another drug and may not reflect the rates observed in practice.

In controlled clinical trials (Study 1 and Study 2), a total of 811 patients with relapsing forms of MS received LEMTRADA. The population was 18 to 55 years of age, 65% were female, and 92% were Caucasian. A total of 811 patients received 1 course of therapy, and 789 patients received a second course of therapy at 12 months. The overall follow-up in the controlled trials was equivalent to 1622 patient years.

In MS clinical studies (controlled and open-label extension), overall, a total of 1217 patients received LEMTRADA. Approximately 60% of patients received a total of 2 treatment courses and approximately 24% of patients received a total of 3 treatment courses; others received a total of 4 or more treatment courses, although data beyond 3 treatment courses are limited. The overall follow-up was 6858 person-years. Patients had a median of 6 years of follow-up from the first LEMTRADA dose, with approximately 14% having at least 7 years of follow-up.

Most Common Adverse Reactions

In controlled clinical trials, the most common adverse reactions with LEMTRADA (in at least 10% of patients and more frequently than in interferon beta-1a) were rash, headache, pyrexia, nasopharyngitis, nausea, urinary tract infection, fatigue, insomnia, upper respiratory tract infection, herpes viral infection, urticaria, pruritus, thyroid gland disorders, fungal infection, arthralgia, pain in extremity, back pain, diarrhea, sinusitis, oropharyngeal pain, paresthesia, dizziness, abdominal pain, flushing, and vomiting.

Table 1 lists adverse reactions occurring in ≥5% of LEMTRADA-treated patients in Study 1 and 2 and at the same or at a higher rate than interferon beta-1a.

Table 1: Adverse Reactions in the Pooled 2-Year Active-Controlled Studies in Patients with Relapsing-Remitting Multiple Sclerosis
 | LEMTRADA (N=811) % | interferon beta-1a 44 mcg (N=389) %
Rash | 53 | 6
Headache | 52 | 23
Pyrexia | 29 | 9
Nasopharyngitis | 25 | 19
Nausea | 21 | 9
Urinary tract infection | 19 | 8
Fatigue | 18 | 13
Insomnia | 16 | 15
Upper respiratory tract infection | 16 | 13
Herpes viral infection | 16 | 3
Urticaria | 16 | 2
Pruritus | 14 | 2
Thyroid gland disorders | 13 | 3
Fungal infection | 13 | 4
Arthralgia | 12 | 9
Pain in extremity | 12 | 9
Back pain | 12 | 8
Diarrhea | 12 | 6
Sinusitis | 11 | 8
Oropharyngeal pain | 11 | 5
Paresthesia | 10 | 8
Dizziness | 10 | 5
Abdominal pain | 10 | 5
Flushing | 10 | 4
Vomiting | 10 | 3
Cough | 9 | 4
Chills | 9 | 3
Dysgeusia | 8 | 7
Influenza | 8 | 6
Dermatitis | 8 | 5
Dyspepsia | 8 | 4
Blood in urine | 8 | 3
Dyspnea | 8 | 1
Tachycardia | 8 | 1
Anxiety | 7 | 6
Muscular weakness | 7 | 6
Bronchitis | 7 | 4
Chest discomfort | 7 | 2
Muscle spasms | 6 | 5
Myalgia | 6 | 5
Decrease in CD4 lymphocytes | 6 | 2
Decrease in CD8 lymphocytes | 6 | 2
Asthenia | 5 | 4
Decrease in T-lymphocyte count | 5 | 3
Erythema | 5 | 2
Peripheral edema | 5 | 2
Epistaxis | 5 | 2
Neck pain | 5 | 2
Abnormal uterine bleeding | 5 | 1

6.2 Lymphopenia

Nearly all (99.9%) patients treated with LEMTRADA in MS clinical trials experienced lymphopenia. The lowest lymphocyte counts occurred approximately by 1 month after each course of treatment. The mean lymphocyte count at 1 month after LEMTRADA treatment was 0.25 × 10^9 L (range 0.02–2.30 × 10^9 L) and 0.32 (0.02–1.81 × 10^9 L) for treatment courses 1 and 2, respectively. Total lymphocyte counts increased to reach the lower limit of normal in approximately 40% of patients by 6 months after each LEMTRADA treatment course and approximately 80% of patients by 12 months after each course [see Clinical Pharmacology (12.2)].

6.3 Suicidal Behavior or Ideation

In clinical studies, 0.6% of patients in both the LEMTRADA and interferon beta-1a groups had events of attempted suicide or suicidal ideation. There were no completed suicides in either clinical study treatment group. Suicidal behavior or ideation occurred in patients with or without a history of a psychiatric or thyroid disorder. Advise patients to report immediately any symptoms of depression or suicidal ideation to the prescribing physician.

6.4 Immunogenicity

As with all therapeutic proteins, there is potential for immunogenicity. The incidence of antibodies is highly dependent on the sensitivity and specificity of the assay. Additionally, the observed incidence of antibody (including inhibitory antibody) positivity in an assay may be influenced by several factors including assay methodology, sample handling, timing of sample collection, concomitant medications, and underlying disease. For these reasons, comparison of the incidence of antibodies to LEMTRADA with the incidence of antibodies to other products may be misleading.

Using an enzyme-linked immunosorbent assay (ELISA) and a competitive binding assay, anti-alemtuzumab binding antibodies were detected in 62%, 67%, and 29% of LEMTRADA-treated patients, at months 1, 3, and 12 (Course 1) as well as 83%, 83%, and 75% of LEMTRADA-treated patients at months 13, 15, and 24 (Course 2). Samples that tested positive for binding antibodies were further evaluated for evidence of in vitro inhibition using a flow cytometry assay. Neutralizing antibodies were detected in 87%, 46%, and 5% of positive binding antibody patients at months 1, 3, and 12 (Course 1) as well as 94%, 88%, and 42% of positive binding antibody patients at months 13, 15, and 24 (Course 2). Anti-alemtuzumab antibodies were associated with decreased alemtuzumab concentration during Course 2, but not Course 1. Through 2 treatment courses, there was no evidence from clinical trials that the presence of binding or inhibitory anti-alemtuzumab antibodies had a significant effect on clinical outcomes, total lymphocyte count, or adverse events. High titer anti-alemtuzumab antibodies, which were observed in 13 patients, were associated with incomplete lymphocyte depletion following a third or fourth treatment course, but there was no clear effect of anti-alemtuzumab antibodies on the clinical efficacy or safety profile of LEMTRADA.

6.5 Postmarketing Experience

The following adverse reactions have been identified during post approval use of alemtuzumab. Because these reactions are reported voluntarily from a population of uncertain size, it is not always possible to reliably estimate their frequency or establish a causal relationship to drug exposure.

Postmarketing Experience with LEMTRADA

Blood and Lymphatic System Disorders: Acquired hemophilia A [see Warnings and Precautions (5.15)], neutropenia, thrombocytopenia [see Warnings and Precautions (5.2)], thrombotic thrombocytopenic purpura [see Warnings and Precautions (5.13)]

Cerebrovascular Disorders: Stroke, including hemorrhagic and ischemic stroke and cervicocephalic arterial dissection [see Warnings and Precautions (5.3)]

Gastrointestinal System Disorders: Cholecystitis, including acalculous cholecystitis and acute acalculous cholecystitis [see Warnings and Precautions (5.19)], immune-mediated colitis [see Warnings and Precautions (5.16)]

Hepatobiliary Disorders: Autoimmune hepatitis [see Warnings and Precautions (5.10)], viral hepatitis [see Warnings and Precautions (5.17)]

Infections and Infestations: Opportunistic infections [see Warnings and Precautions (5.17)], Progressive multifocal leukoencephalopathy [see Warnings and Precautions (5.18)]

Immune System Disorders: Autoimmune hepatitis, vasculitis, Guillain-Barré syndrome [see Warnings and Precautions (5.1)], hemophagocytic lymphohistiocytosis [see Warnings and Precautions (5.11)], sarcoidosis

Musculoskeletal and Connective Tissue Disorders: Adult Onset Still's Disease [see Warnings and Precautions (5.12)]

Nervous System Disorders: Autoimmune encephalitis [see Warnings and Precautions (5.14)], myasthenia gravis, Lambert-Eaton myasthenic syndrome

Pulmonary System Disorders: Pulmonary alveolar hemorrhage [see Warnings and Precautions (5.2)]

Skin and Subcutaneous Tissue Disorders: Alopecia

Postmarketing Experience with CAMPATH

CAMPATH is approved for the treatment of B-cell chronic lymphocytic leukemia (B-CLL) and is generally administered at higher and more frequent doses (e.g., 30 mg) than recommended in the treatment of MS.

Cardiac Disorders: Congestive heart failure, cardiomyopathy, and decreased ejection fraction in non-MS patients previously treated with potentially cardiotoxic agents.

8 USE IN SPECIFIC POPULATIONS

8.1 Pregnancy

Risk Summary

There are no adequate data on the developmental risk associated with the use of LEMTRADA in pregnant women. LEMTRADA was embryolethal in pregnant huCD52 transgenic mice when administered during organogenesis [see Animal data]. Auto-antibodies may develop after administration of LEMTRADA. Placental transfer of anti-thyroid antibodies resulting in neonatal Graves' disease has been reported.

In the U.S. general population, the estimated background risk of major birth defects and miscarriage in clinically recognized pregnancies is 2% to 4% and 15% to 20%, respectively. The background risk of major birth defects and miscarriage for the indicated population is unknown.

There is a pregnancy surveillance program for LEMTRADA. If LEMTRADA exposure occurs during pregnancy, healthcare providers and patients are encouraged to report pregnancies by calling 1-800-745-4447, option 2.

Clinical Considerations

LEMTRADA induces persistent thyroid disorders [see Warnings and Precautions (5.8)]. Untreated hypothyroidism in pregnant women increases the risk for miscarriage and may have effects on the fetus including mental retardation and dwarfism. In mothers with Graves' disease, maternal thyroid stimulating hormone receptor antibodies can be transferred to a developing fetus and can cause neonatal Graves' disease. In a patient who developed Graves' disease after treatment with alemtuzumab, placental transfer of anti-thyrotropin receptor antibodies resulted in neonatal Graves' disease with thyroid storm in her infant who was born 1 year after alemtuzumab dosing [see Warnings and Precautions (5.1)].

Data

Animal data

When LEMTRADA was administered to pregnant huCD52 transgenic mice during organogenesis (gestation days [GD] 6–10 or GD 11–15) at doses of 3 or 10 mg/kg IV, no teratogenic effects were observed. However, there was an increase in embryolethality (increased postimplantation loss and the number of dams with all fetuses dead or resorbed) in pregnant animals dosed during GD 11–15. In a separate study in pregnant huCD52 transgenic mice, administration of LEMTRADA during organogenesis (GD 6–10 or GD 11–15) at doses of 3 or 10 mg/kg IV, decreases in B- and T-lymphocyte populations were observed in the offspring at both doses tested.

In pregnant huCD52 transgenic mice administered LEMTRADA at doses of 3 or 10 mg/kg/day IV throughout gestation and lactation, there was an increase in pup deaths during the lactation period at 10 mg/kg. Decreases in T- and B-lymphocyte populations and in antibody response were observed in offspring at both doses tested.

8.2 Lactation

Risk Summary

There are no data on the presence of alemtuzumab in human milk, the effects on the breastfed infant, or the effects of the drug on milk production. Alemtuzumab was detected in the milk of lactating huCD52 transgenic mice administered LEMTRADA [see Animal data].

The developmental and health benefits of breastfeeding should be considered along with the mother's clinical need for LEMTRADA and any potential adverse effects on the breastfed child from LEMTRADA or from the underlying maternal conditions.

Data

Animal data

Alemtuzumab was detected in the milk of lactating huCD52 transgenic mice following intravenous administration of LEMTRADA at a dose of 10 mg/kg on postpartum days 8–12. Serum levels of alemtuzumab were similar in lactating mice and offspring on postpartum Day 13 and were associated with evidence of pharmacological activity (decrease in lymphocyte counts) in the offspring.

8.3 Females and Males of Reproductive Potential

Contraception

Before initiation of LEMTRADA treatment, women of childbearing potential should be counselled on the potential for a serious risk to the fetus. To avoid in utero exposure to LEMTRADA, women of childbearing potential should use effective contraceptive measures when receiving a course of treatment with LEMTRADA and for 4 months following that course of treatment [see Use in Specific Populations (8.1)].

Infertility

In huCD52 transgenic mice, administration of LEMTRADA prior to and during the mating period resulted in adverse effects on sperm parameters in males and reduced number of corpora lutea and implantations in females [see Nonclinical Toxicology (13.1)].

8.4 Pediatric Use

Safety and effectiveness in pediatric patients less than 17 years of age have not been established. Use of LEMTRADA is not recommended in pediatric patients due to the risks of autoimmunity, infusion reactions, and stroke, and because it may increase the risk of malignancies (thyroid, melanoma, lymphoproliferative disorders, and lymphoma) [see Warnings and Precautions (5.1, 5.2, 5.3, 5.4)].

8.5 Geriatric Use

Clinical studies of LEMTRADA did not include sufficient numbers of patients aged 65 and over to determine whether they respond differently than younger patients.

10 OVERDOSAGE

Two MS patients experienced serious reactions (headache, rash, and either hypotension or sinus tachycardia) after a single accidental infusion up to 60 mg of LEMTRADA. Doses of LEMTRADA greater than those recommended may increase the intensity and/or duration of infusion reactions or its immune effects. There is no known antidote for alemtuzumab overdosage.

11 DESCRIPTION

Alemtuzumab is a recombinant humanized IgG1 kappa monoclonal antibody directed against the cell surface glycoprotein, CD52. Alemtuzumab has an approximate molecular weight of 150 kD. Alemtuzumab is produced in mammalian cell (Chinese hamster ovary) suspension culture in a nutrient medium containing neomycin. Neomycin is not detectable in the final product.

LEMTRADA (alemtuzumab) injection is a sterile, clear and colorless to slightly yellow, solution (pH 7.2 ± 0.2) for intravenous infusion.

Each 1 mL of solution contains 10 mg alemtuzumab, dibasic sodium phosphate (1.15 mg), disodium edetate dihydrate (0.0187 mg), polysorbate 80 (0.1 mg), potassium chloride (0.2 mg), potassium dihydrogen phosphate (0.2 mg), sodium chloride (8 mg), and Water for Injection, USP.

12 CLINICAL PHARMACOLOGY

12.1 Mechanism of Action

The precise mechanism by which alemtuzumab exerts its therapeutic effects in multiple sclerosis is unknown but is presumed to involve binding to CD52, a cell surface antigen present on T and B lymphocytes, and on natural killer cells, monocytes, and macrophages. Following cell surface binding to T and B lymphocytes, alemtuzumab results in antibody-dependent cellular cytolysis and complement-mediated lysis.

12.2 Pharmacodynamics

Effects of LEMTRADA on the Lymphocyte Population

LEMTRADA depletes circulating T and B lymphocytes after each treatment course. In clinical trials, the lowest cell counts occurred 1 month after a course of treatment at the time of the first post-treatment blood count. Lymphocyte counts then increased over time: B cell counts usually recovered within 6 months; T cell counts increased more slowly and usually remained below baseline 12 months after treatment. Approximately 60% of patients had total lymphocyte counts below the lower limit of normal 6 months after each treatment course and 20% had counts below the lower limit of normal after 12 months.

Reconstitution of the lymphocyte population varies for the different lymphocyte subtypes. At Month 1 in clinical trials, the mean CD4+ lymphocyte count was 40 cells per microliter, and, at Month 12, 270 cells per microliter. At 30 months, approximately half of patients had CD4+ lymphocyte counts that remained below the lower limit of normal.

Cardiac Electrophysiology

In a study of 53 MS patients, alemtuzumab 12 mg per day for 5 days caused no changes in the QTc interval greater than 20 ms. An average 22 to 26 beats-per-minute increase in heart rate was observed for at least 2 hours after the first but not subsequent infusions.

12.3 Pharmacokinetics

The pharmacokinetics of LEMTRADA were evaluated in a total of 148 patients with relapsing forms of MS who received 12 mg/day on 5 consecutive days, followed by 12 mg/day on 3 consecutive days 12 months following the first treatment course.

Absorption

Serum concentrations increased with each consecutive dose within a treatment course, with the highest observed concentrations occurring following the last infusion of a treatment course. The mean maximum concentration was 3014 ng/mL on Day 5 of the first treatment course, and 2276 ng/mL on Day 3 of the second treatment course.

Distribution

LEMTRADA is largely confined to the blood and interstitial space with a central volume of distribution of 14.1 L.

Elimination

The elimination half-life was approximately 2 weeks and was comparable between courses. The serum concentrations were generally undetectable (<60 ng/mL) within approximately 30 days following each treatment course.

Specific Populations

Age, race, or gender had no effect on the pharmacokinetics of LEMTRADA.

13 NONCLINICAL TOXICOLOGY

13.1 Carcinogenesis, Mutagenesis, Impairment of Fertility

Studies to assess the carcinogenic or genotoxic potential of LEMTRADA have not been conducted.

When LEMTRADA (3 or 10 mg/kg IV) was administered to huCD52 transgenic male mice on 5 consecutive days prior to cohabitation with untreated wild-type females, no effect on fertility or reproductive performance was observed. However, adverse effects on sperm parameters (including abnormal morphology [detached/no head] and reduced total count and motility) were observed at both doses tested.

When LEMTRADA (3 or 10 mg/kg IV) was administered to huCD52 transgenic female mice for 5 consecutive days prior to cohabitation with untreated wild-type males, there was a decrease in the average number of corpora lutea and implantation sites and an increase in postimplantation loss, resulting in fewer viable embryos at the higher dose tested.

14 CLINICAL STUDIES

The efficacy of LEMTRADA was demonstrated in two studies (Study 1 and 2) that evaluated LEMTRADA 12 mg in patients with relapsing-remitting multiple sclerosis (RRMS). LEMTRADA was administered by intravenous infusion once daily over a 5-day course, followed one year later by intravenous infusion once daily over a 3-day course. Both studies included patients who had experienced at least 2 relapses during the 2 years prior to trial entry and at least 1 relapse during the year prior to trial entry. Neurological examinations were performed every 12 weeks and at the time of suspected relapse. Magnetic resonance imaging (MRI) evaluations were performed annually.

Study 1

Study 1 was a 2-year randomized, open-label, rater-blinded, active comparator (interferon beta-1a 44 micrograms administered subcutaneously three times a week) controlled study in patients with RRMS. Patients entering Study 1 had Expanded Disability Status Scale (EDSS) scores of 5 or less and had to have experienced at least one relapse while on interferon beta or glatiramer acetate therapy.

Patients were randomized to receive LEMTRADA (n=426) or interferon beta-1a (n=202). At baseline, the mean age was 35 years, the mean disease duration was 4.5 years, and the mean EDSS score was 2.7.

The clinical outcome measures were the annualized relapse rate (ARR) over 2 years and the time to confirmed disability progression. Confirmed disability progression was defined as at least a 1 point increase above baseline EDSS (1.5 point increase for patients with baseline EDSS of 0) sustained for 6 months. The MRI outcome measure was the change in T2 lesion volume.

The annualized relapse rate was significantly lower in patients treated with LEMTRADA than in patients who received interferon beta-1a. Time to onset of 6-month confirmed disability progression was significantly delayed with LEMTRADA treatment compared to interferon beta-1a. There was no significant difference between the treatment groups for the change in T2 lesion volume. The results of Study 1 are shown in Table 2 and Figure 1.

Table 2: Clinical and MRI Results of Study 1
 | LEMTRADA | interferon beta-1a 44 mcg | p-value
 | (N=426) | (N=202)
Clinical Outcomes
Annualized relapse rate | 0.26 | 0.52 | <0.0001
Relative reduction | 49%
Proportion of patients with disability progression at Year 2 | 13% | 21% | 0.0084
Relative risk reduction | 42%
Percent of patients remaining relapse-free at Year 2 | 65% | 47% | <0.0001
MRI Outcomes
Percent change in T2 lesion volume from baseline | -1.3 | -1.2 | 0.14

Figure 1: Time to 6-month Confirmed Disability Progression (Study 1)

Study 2

Study 2 was a 2-year randomized, open-label, rater-blinded, active comparator (interferon beta-1a 44 micrograms administered subcutaneously three times a week) controlled study in patients with RRMS. Patients entering Study 2 had EDSS scores of 3 or less and no prior treatment for multiple sclerosis.

Patients were randomized to receive LEMTRADA (n=376) or interferon beta-1a (n=187). At baseline, the mean age was 33 years, the mean disease duration was 2 years, and the mean EDSS score was 2.

The clinical outcome measures were the annualized relapse rate (ARR) over 2 years and the time to confirmed disability progression, as defined in Study 1. The MRI outcome measure was the change in T2 lesion volume.

The annualized relapse rate was significantly lower in patients treated with LEMTRADA than in patients who received interferon beta-1a. There was no significant difference between the treatment groups for the time to confirmed disability progression and for the primary MRI endpoint (change in T2 lesion volume). The results for Study 2 are shown in Table 3.

Table 3: Clinical and MRI Results of Study 2
 | LEMTRADA | interferon beta-1a 44 mcg | p-value
 | (N=376) | (N=187)
Clinical Outcomes
Annualized relapse rate Relative reduction | 0.18 55% | 0.39 | <0.0001
Proportion of patients with disability progression at Year 2 Relative risk reduction | 8% 30% | 11% | 0.22
Percent of patients remaining relapse-free at Year 2 | 78% | 59% | <0.0001
MRI Outcomes
Percent change in T2 lesion volume from baseline | -9.3 | -6.5 | 0.31

16 HOW SUPPLIED/STORAGE AND HANDLING

16.1 How Supplied

LEMTRADA (alemtuzumab) injection is a sterile, clear and colorless to slightly yellow solution for intravenous infusion, containing no antimicrobial preservatives.

Each LEMTRADA carton (NDC: 58468-0200-1) contains one single-dose vial that delivers 12 mg/1.2 mL (10 mg/mL). The vial stopper is not made with natural rubber latex.

16.2 Storage and Handling

Store LEMTRADA vials at 2°C to 8°C (36°F to 46°F). Do not freeze or shake. Store in original carton to protect from light.

17 PATIENT COUNSELING INFORMATION

Advise the patient to read the FDA-approved patient labeling (Medication Guide).

Autoimmunity

- Advise patients to contact their healthcare provider promptly if they experience any symptoms of potential autoimmune disease. Give examples of important symptoms such as bleeding, easy bruising, petechiae, purpura, hematuria, edema, jaundice, or hemoptysis [see Warnings and Precautions (5.1)].
- Advise patients of the importance of monthly blood and urine tests for 48 months following the last course of LEMTRADA to monitor for signs of autoimmunity because early detection and prompt treatment can help prevent serious and potentially fatal outcomes associated with these events. Advise patients that monitoring may need to continue past 48 months if they have signs or symptoms of autoimmunity.
- Advise patients that LEMTRADA may cause hyperthyroid or hypothyroid disorders.
- Advise patients to contact their healthcare provider if they experience symptoms reflective of a potential thyroid disorder such as unexplained weight loss or gain, fast heartbeat or palpitations, nervousness, worsening tiredness, eye swelling, constipation, or feeling cold.
- Advise women of childbearing potential of the risks of pregnancy with concomitant thyroid disease. Advise women of childbearing potential to discuss pregnancy planning with their doctor.
- Cases of autoimmune hepatitis have been reported in patients treated with LEMTRADA. Advise patients to contact their healthcare provider right away if they develop signs or symptoms suggestive of hepatic dysfunction such as unexplained nausea, vomiting, abdominal pain, fatigue, anorexia, jaundice and/or dark urine, or bleeding or bruising more easily than normal.
- Advise patients to contact their healthcare provider if they experience symptoms of acquired hemophilia A such as spontaneous bruising, nose bleeds, painful or swollen joints, other types of bleeding, or bleeding from a cut that may take longer than usual to stop.
- Advise patients that cases of autoimmune encephalitis can occur after receiving LEMTRADA. This condition may include symptoms such as behavior and psychiatric changes, movement disorders, short-term memory loss or seizures, as well as other symptoms that may resemble an MS relapse.

Infusion Reactions

- Advise patients that infusion reactions can occur at the time of infusion or after they leave the infusion center [see Warnings and Precautions (5.2)].
- Instruct the patient to remain at the infusion center for at least 2 hours after each LEMTRADA infusion, or longer at the discretion of the healthcare provider. Advise patients that symptoms of infusion reactions may occur after they leave the infusion center and to report these symptoms to their healthcare provider.
- Advise patients that their healthcare provider will monitor vital signs, including blood pressure, before and during the infusion and to contact their healthcare provider promptly if they experience infusion reactions, which include swelling in the mouth or throat, difficulty breathing, weakness, abnormal heart rate (fast, slow, or irregular), chest pain, rash, facial drooping, sudden severe headache, weakness on one side of the body, difficulty with speech, or neck pain.
- Instruct patients that there have also been reports of rare but serious infusion reactions, including bleeding in the lung, chest tightness/pain or discomfort, heart attack, and stroke or tears in blood vessels supplying the brain, which should be reported to your healthcare provider.
- Advise patients that reactions may occur following any of the doses during the treatment course. In the majority of cases, reactions occurred within 1–3 days of the infusion.

Stroke and Cervicocephalic Arterial Dissection

- Educate patients on the symptoms and instruct patients to seek immediate medical attention if symptoms of stroke or cervicocephalic arterial dissection occur (e.g., neck pain, weakness on one side, facial droop, difficulty with speech, sudden severe headache) [see Warnings and Precautions (5.3)].

Malignancies

- Advise patients that LEMTRADA may increase their risk of malignancies including thyroid cancer and melanoma [see Warnings and Precautions (5.4)].
- Advise patients to report symptoms of thyroid cancer, including a new lump or swelling in the neck, pain in the front of the neck, hoarseness or other voice changes that do not go away, trouble swallowing or breathing, or a constant cough not due to a cold.
- Advise patients that they should have baseline and yearly skin examinations.

LEMTRADA REMS Program

- LEMTRADA is available only through a restricted program called the LEMTRADA REMS Program [see Warnings and Precautions (5.5)]. Inform the patient of the following notable requirements:
  - Patients and providers must be enrolled in the program.
  - Patients must comply with the ongoing monitoring requirements.
  - Patients must report any side effects or symptoms to their doctor.
- LEMTRADA is available only at certified infusion centers participating in the program. Therefore, provide patients with information on the LEMTRADA REMS Program in order to locate an infusion center.
- Advise patients to read the LEMTRADA REMS material for patients, LEMTRADA Treatment and Infusion Reactions Patient Guide.
- Instruct patients to carry the LEMTRADA REMS Patient Safety Information Card with them in case of an emergency.

Hemophagocytic Lymphohistiocytosis

- Inform patients that treatment with LEMTRADA may increase the risk of a type of excessive immune activation (hemophagocytic lymphohistiocytosis), which can be fatal, particularly if not diagnosed and treated early.
- Advise patients to contact their healthcare provider immediately if they experience symptoms such as fever, swollen glands, skin rash, or new neurologic symptoms such as mental status changes, ataxia, or seizures.
- In cases reported with LEMTRADA, symptoms occurred within approximately thirteen months to thirty-three months following the initiation of treatment.

Adult Onset Still's Disease (AOSD)

- Inform patients that AOSD is a rare condition that has the potential to cause multi-organ inflammation with several symptoms such as fever >39°C or 102.2°F lasting more than 1 week, pain, stiffness with or without swelling in multiple joints, and/or a skin rash [see Warnings and Precautions (5.12)].
- Instruct patients if they experience a combination of these symptoms to contact their healthcare provider immediately.

Thrombotic Thrombocytopenic Purpura

- Inform patients that there have been reports of TTP in patients treated with LEMTRADA and that this is a potentially life-threatening condition [see Warnings and Precautions (5.13)].
- Instruct patients to get prompt medical attention if they experience symptoms of TTP such as fever, fatigue, pallor, purpura, jaundice, tachycardia, dyspnea, hematuria, dark-colored urine, decreased urine volume, abdominal pain, nausea, vomiting, or new neurological symptoms such as confusion, altered mental status, vision or speech changes, or seizures.

Immune-Mediated Colitis

- Advise patients to promptly contact their healthcare provider if they experience any signs and symptoms of colitis, including diarrhea, abdominal pain, and blood in stool [see Warnings and Precautions (5.16)].

Infections

- Advise patients to contact their healthcare provider if they develop symptoms of serious infection such as fatigue, fever, or swollen glands [see Warnings and Precautions (5.17)].
- Advise patients to complete any necessary immunizations at least 6 weeks prior to treatment with LEMTRADA [see Dosage and Administration (2.1)]. Advise patients that they should talk to their healthcare provider before taking any vaccine after recent treatment with LEMTRADA [see Warnings and Precautions (5.17)].
- Advise patients to avoid or adequately heat foods that are potential sources of Listeria monocytogenes prior to receiving LEMTRADA and if they have had a recent course of LEMTRADA. The duration of increased risk for Listeria infection after LEMTRADA administration is not known. Inform patients that Listeria infection can lead to significant complications or death [see Warnings and Precautions (5.17)].
- Advise patients to take their prescribed medication for herpes prophylaxis as directed by their healthcare provider [see Warnings and Precautions (5.17)].
- Advise patients that yearly HPV screening is recommended [see Warnings and Precautions (5.17)].

Progressive Multifocal Leukoencephalopathy

- Inform patients that progressive multifocal leukoencephalopathy (PML) has occurred in a patient who received LEMTRADA. Inform the patient that PML is characterized by a progression of deficits and usually leads to death or severe disability over weeks or months. Instruct the patient of the importance of contacting their doctor if they develop any symptoms suggestive of PML. Inform the patient that typical symptoms associated with PML are diverse, progress over days to weeks, and include progressive weakness on one side of the body or clumsiness of limbs, disturbance of vision, and changes in thinking, memory, and orientation leading to confusion and personality changes [see Warnings and Precautions (5.18)].

Acute Acalculous Cholecystitis

- Advise patients to report symptoms of acute acalculous cholecystitis. These include abdominal pain, abdominal tenderness, fever, nausea, and vomiting [see Warnings and Precautions (5.19)].

Pneumonitis

- Advise patients that pneumonitis has been reported in patients treated with LEMTRADA [see Warnings and Precautions (5.20)]. Advise patients to report symptoms of lung disease such as shortness of breath, cough, wheezing, chest pain or tightness, and hemoptysis.

Concomitant Use of CAMPATH

- Advise patients that alemtuzumab is the same drug as CAMPATH for use in B-CLL. Patients should inform their healthcare provider if they have taken CAMPATH [see Warnings and Precautions (5.21)].

Fetal Risk

- Inform patients that LEMTRADA may cause fetal harm. Discuss with women of childbearing age whether they are pregnant, might be pregnant, or are trying to become pregnant. Advise women of childbearing age of the need for effective contraception during LEMTRADA treatment and for 4 months after a treatment course of LEMTRADA. Advise the patient that if she should nevertheless become pregnant, she should immediately inform her physician.
- Advise patients exposed to LEMTRADA during pregnancy that there is a pregnancy safety surveillance program that monitors pregnancy outcomes [see Use in Specific Populations (8.1)]. If exposure occurs during pregnancy, healthcare providers and patients are encouraged to report pregnancies by calling 1-800-745-4447, option 2.

Manufactured and distributed by:
Genzyme Corporation
Cambridge, MA 02141
A SANOFI COMPANY
US License Number: 1596

LEMTRADA and CAMPATH are registered trademarks of Genzyme Corporation. ©2024 Genzyme Corporation.

MEDICATION GUIDE
LEMTRADA® (lem-TRA-da)
(alemtuzumab), injection for intravenous infusion

Read this Medication Guide before you start receiving LEMTRADA and before you begin each treatment course. There may be new information. This information does not take the place of talking to your healthcare provider about your medical condition or treatment.

What is the most important information I should know about LEMTRADA?

LEMTRADA can cause serious side effects, including:

1. Serious autoimmune problems. Some people receiving LEMTRADA develop a condition where the immune cells in your body attack other cells or organs in the body (autoimmunity) which can be serious and may cause death. Serious autoimmune problems may include:

- immune thrombocytopenic purpura (ITP). LEMTRADA may cause the number of platelets in your blood to be reduced (ITP). ITP can cause severe bleeding that may cause life-threatening problems. Call your healthcare provider right away if you have any of the following symptoms:

- easy bruising
- bleeding from a cut that is hard to stop
- coughing up blood
- heavier menstrual periods than normal

- bleeding from your gums or nose that is new or takes longer than usual to stop
- small, scattered spots on your skin that are red, pink, or purple

- kidney problems. LEMTRADA may cause a serious kidney problem called anti-glomerular basement membrane disease. If this happens and you do not get treated, anti-glomerular basement membrane disease can lead to severe kidney damage, kidney failure that needs dialysis, a kidney transplant, or death. Call your healthcare provider right away if you have any of the following symptoms:

- swelling of your legs or feet
- blood in the urine (red or tea-colored urine)

- decrease in urine
- fatigue
- coughing up blood

Side effects may happen while you receive LEMTRADA and for 4 years after you stop receiving LEMTRADA. Your healthcare provider will order blood and urine tests before you receive, while you are receiving, and every month for 4 years after you receive your last LEMTRADA infusion. You may need to continue these blood and urine tests after 4 years if you have any autoimmune signs or symptoms. The blood and urine tests will help your healthcare provider watch for signs and symptoms of serious autoimmune problems.

It is important to have your blood and urine tested, even if you are feeling well and do not have any symptoms from LEMTRADA and your multiple sclerosis. This may help your healthcare provider find any problems early.

2. Serious infusion reactions. LEMTRADA can cause serious infusion reactions that may cause death. Serious infusion reactions may happen while you receive, or up to 24 hours or longer after you receive LEMTRADA.
  You will receive your infusion at a healthcare facility with equipment and staff trained to manage infusion reactions. You will be watched while you receive and for at least 2 hours after you receive LEMTRADA. It is important that you stay at the infusion center for at least 2 hours after your infusion is finished or longer if your healthcare provider decides you need to stay longer. If a serious infusion reaction happens while you are receiving LEMTRADA, your infusion may be stopped.
  Tell your healthcare provider right away if you have any of the following symptoms of a serious infusion reaction during the infusion, and after you have left the healthcare facility:

- swelling in your mouth or throat
- trouble breathing
- weakness

- fast, slow, or irregular heartbeat
- chest pain
- rash

To lower your chances of getting a serious infusion reaction, your healthcare provider will give you a medicine called corticosteroids before your first 3 infusions of a treatment course. You may also be given other medicines before or after the infusion to try to reduce your chances of these reactions or to treat them after they happen.

3. Stroke and tears in your arteries that supply blood to your brain (carotid and vertebral arteries). Some people have had serious and sometimes deadly strokes and tears in their carotid or vertebral arteries within 3 days of receiving LEMTRADA. Get help right away if you have any of the following symptoms that may be signs of a stroke or tears in your carotid or vertebral arteries:

- drooping of parts of your face
- sudden severe headache
- neck pain

- weakness on one side
- difficulty with speech

4. Certain cancers. Receiving LEMTRADA may increase your chance of getting some kinds of cancers, including thyroid cancer, skin cancer (melanoma), and blood cancers called lymphoproliferative disorders and lymphoma. Call your healthcare provider if you have the following symptoms that may be a sign of thyroid cancer:

- new lump
- swelling in your neck
- pain in the front of your neck
- hoarseness or other voice changes that do not go away

- trouble swallowing or breathing
- cough that is not caused by a cold

You should have your skin checked before you start receiving LEMTRADA and each year while you are receiving treatment to monitor symptoms of skin cancer.

Because of your risk of autoimmunity, infusion reactions, and the risk of some kinds of cancers, LEMTRADA is only available through a restricted program called the LEMTRADA Risk Evaluation and Mitigation Strategy (REMS) Program. Call 1-855-676-6326 to enroll in the LEMTRADA REMS Program.

- You and your healthcare provider must be enrolled in the LEMTRADA REMS Program.
- LEMTRADA can only be given at a certified healthcare facility that participates in the LEMTRADA REMS Program. Your healthcare provider can give you information on how to find a certified healthcare facility.
- Read the LEMTRADA REMS "LEMTRADA Treatment and Infusion Reactions Patient Guide" after you are enrolled in the program.
- Carry your LEMTRADA REMS Patient Safety Information Card with you in case of an emergency.

What is LEMTRADA?

LEMTRADA is a prescription medicine used to treat relapsing forms of multiple sclerosis (MS), to include relapsing-remitting disease and active secondary progressive disease, in adults. Since treatment with LEMTRADA can increase your risk of getting certain conditions and diseases, LEMTRADA is generally prescribed for people who have tried 2 or more MS medicines that have not worked well enough. LEMTRADA is not recommended for use in patients with clinically isolated syndrome (CIS).

It is not known if LEMTRADA is safe and effective for use in children under 17 years of age.

Who should not receive LEMTRADA?

Do not receive LEMTRADA if you:

- are allergic to alemtuzumab or to any of the inactive ingredients in LEMTRADA. See the end of this Medication Guide for a complete list of ingredients in LEMTRADA.
- are infected with human immunodeficiency virus (HIV).
- have an active infection.

What should I tell my healthcare provider before receiving LEMTRADA?

Before receiving LEMTRADA, tell your healthcare provider if you:

- have bleeding problems.
- have thyroid problems.
- have kidney problems.
- have a recent history of infection.
- are taking a medicine called CAMPATH®. Alemtuzumab, the active ingredient in LEMTRADA, is the same drug as CAMPATH.
- have received a live vaccine in the past 6 weeks before receiving LEMTRADA or plan to receive any live vaccines. Ask your healthcare provider if you are not sure if your vaccine is a live vaccine.
- are pregnant or plan to become pregnant. LEMTRADA may harm your unborn baby.
  - There is a pregnancy surveillance program for people who are exposed to LEMTRADA during pregnancy. The purpose of the program is to collect information about the health of pregnant people exposed to LEMTRADA and their babies. If you become pregnant, inform your healthcare provider.
- you should use birth control while receiving LEMTRADA and for 4 months after your course of treatment.
- are breastfeeding or plan to breastfeed. It is not known if LEMTRADA passes into your breast milk. You and your healthcare provider should decide if you should receive LEMTRADA or breastfeed.

Tell your healthcare provider about all the medicines you take, including prescription and over-the-counter medicines, vitamins, and herbal supplements.

LEMTRADA and other medicines may affect each other causing side effects. Especially tell your healthcare provider if you take medicines that increase your chance of getting infections, including medicines used to treat cancer or to control your immune system.

Know the medicines you take. Keep a list of them to show your healthcare provider and pharmacist when you get a new medicine.

How will I receive LEMTRADA?

- LEMTRADA is given through a needle placed in your vein (IV infusion).
- It takes about 4 hours to receive a full dose of LEMTRADA each day.
- You will receive LEMTRADA over 2 or more treatment courses.
- You will receive LEMTRADA for 5 days in a row (consecutive) for the first treatment course and then for 3 days in a row (consecutive) about 1 year later for your second treatment course.
- Additional LEMTRADA treatment courses, if needed, may be given for 3 days in a row (consecutive) at least 1 year after the prior treatment course.

What are the possible side effects of LEMTRADA?

LEMTRADA may cause serious side effects including:

- see "What is the most important information I should know about LEMTRADA?"
- thyroid problems. Some people who receive LEMTRADA may get thyroid problems including an overactive thyroid (hyperthyroidism) or an underactive thyroid (hypothyroidism). Your healthcare provider will do blood tests to check how your thyroid is working. Call your healthcare provider if you have any of the symptoms of thyroid problems.
  - Symptoms of hyperthyroidism may include:

- excessive sweating
- unexplained weight loss
- fast heartbeat

- eye swelling
- nervousness

- Symptoms of hypothyroidism may include:

- unexplained weight gain
- feeling cold

- worsening tiredness
- constipation

- low blood counts (cytopenias). LEMTRADA may cause a decrease in some types of blood cells. Some people with these low blood counts have increased infections. Symptoms of cytopenias may include:

- weakness
- chest pain
- yellowing of the skin or whites of eyes (jaundice)

- dark urine
- fast heartbeat

Your healthcare provider will do blood tests to check for cytopenias. Call your healthcare provider right away if you have symptoms listed above.

- inflammation of the liver. Call your healthcare provider right away if you have symptoms such as unexplained nausea, stomach pain, tiredness, loss of appetite, yellowing of skin or whites of eyes, or bleeding or bruising more easily than normal.
- hemophagocytic lymphohistiocytosis (HLH). LEMTRADA may increase the risk of a type of overactivity of the immune system (hemophagocytic lymphohistiocytosis) that can be fatal, especially if not diagnosed and treated early. Call your healthcare provider right away if you have symptoms such as fever, swollen glands, skin rash, or new nervous system problems, such as seizures, changes in your thinking or level of alertness, or new or worsening unsteadiness or trouble walking. These symptoms have happened in people taking LEMTRADA about 13 months to 33 months after they started taking LEMTRADA.
- adult onset still's disease (AOSD). Adult onset still's disease (AOSD) is a rare condition that can cause a high fever lasting more than 1 week, pain, stiffness with or without swelling in multiple joints, and/or a skin rash. If you experience a combination of these symptoms, contact your healthcare provider immediately.
- thrombotic thrombocytopenic purpura (TTP). Thrombotic thrombocytopenic purpura (TTP) can occur with LEMTRADA. TTP is a blood clotting problem where blood clots can form in blood vessels anywhere in the body. TTP needs to be treated in a hospital right away, because it can cause death. Get medical help right away if you have any of these symptoms:

- purplish spots (called purpura) on the skin or in the mouth (mucous membranes) due to bleeding under the skin
- your skin or the whites of your eyes are yellow (jaundice)
- you feel tired or weak
- your skin looks very pale
- fever
- fast heart rate or feeling short of breath

- headache
- speech changes
- confusion
- vision changes
- seizure
- low amount of urine or dark urine, or urine that has blood in it
- stomach area (abdominal) pain
- nausea, vomiting, or diarrhea

- autoimmune encephalitis (AIE). Autoimmune encephalitis (AIE), a brain disorder, can occur after receiving LEMTRADA and may include symptoms that may seem like an MS relapse. Call your healthcare provider right away if you have any of the following symptoms:

- personality changes
- mood changes
- agitation
- seeing things that are not there (hallucinations)

- short term memory loss
- confusion
- movement disorders
- seizure

- bleeding disorder (acquired hemophilia A). LEMTRADA may cause a bleeding disorder called acquired hemophilia A. Call your healthcare provider right away if you have any of the following symptoms:

- bruising
- nose bleeds
- painful or swollen joints

- blood in urine
- dark or bloody stools
- bleeding from a cut that may take longer than usual to stop

- inflammation of the colon (colitis):
  Tell your healthcare provider if you have any symptoms of colitis, such as:
  - diarrhea (loose stools) or more frequent bowel movements than usual
  - stools that are black, tarry, sticky or have blood or mucous
  - severe stomach-area (abdomen) pain or tenderness

- serious infections. LEMTRADA may cause you to have serious infections while you receive and after receiving a treatment course. Serious infections may include:
  - listeria. People who receive LEMTRADA have an increased chance of getting an infection caused by the bacteria, listeria, which can lead to significant complications or death. Avoid foods that may be a source for listeria (for example, deli meat, unpasteurized milk and cheese products, soft cheeses, or undercooked meat, seafood or poultry) or make sure that the food you eat which may contain listeria is heated well if you receive treatment with LEMTRADA.
  - herpes viral infections. Some people taking LEMTRADA have an increased chance of getting herpes viral infections. Your healthcare provider will prescribe medicines to reduce your chances of getting these infections. Take these medicines exactly as your healthcare provider tells you to.
  - human papilloma virus (HPV). Females have an increased chance of getting a cervical HPV infection. If you are a female, you should have an HPV screening each year.
  - tuberculosis. Your healthcare provider should check you for tuberculosis before you receive LEMTRADA.
  - fungal infections.

Call your healthcare provider right away if you have symptoms of a serious infection, such as fever or swollen glands. You may need to go to the hospital for treatment if you get a serious infection. It is important to tell the healthcare providers that you have received LEMTRADA.

Talk to your healthcare provider before you get vaccinations after receiving LEMTRADA. Certain vaccinations may increase your chances of getting infections.

- Progressive multifocal leukoencephalopathy (PML). A rare brain infection that usually leads to death or severe disability has been reported with LEMTRADA. Symptoms of PML get worse over days to weeks. It is important that you call your doctor right away if you have any new or worsening medical problems that have lasted several days, including problems with:

- thinking
- eyesight
- strength

- balance
- weakness on 1 side of your body
- using your arms or legs

- Inflammation of the gallbladder without gallstones (acalculous cholecystitis). LEMTRADA may increase your chance of getting inflammation of the gallbladder without gallstones, a serious medical condition that can be life-threatening. Call your healthcare provider right away if you have any of the following symptoms of acalculous cholecystitis, which may include:

- stomach pain or discomfort
- fever

- nausea or vomiting

- swelling of lung tissue (pneumonitis). Some people have had swelling of the lung tissue while receiving LEMTRADA. Call your healthcare provider right away if you have the following symptoms:

- shortness of breath
- cough
- wheezing

- chest pain or tightness
- coughing up blood

The most common side effects of LEMTRADA include:

- rash
- headache
- thyroid problems
- fever
- swelling of your nose and throat (nasopharyngitis)
- nausea
- urinary tract infection
- feeling tired
- trouble sleeping
- upper respiratory tract infection
- herpes viral infection
- hives
- itching

- fungal infection
- joint pain
- pain in your arms or legs
- back pain
- diarrhea
- sinus infection
- mouth pain or sore throat
- tingling sensation
- dizziness
- stomach pain
- sudden redness in face, neck, or chest
- vomiting

Tell your healthcare provider if you have any side effect that bothers you or that does not go away.

These are not all the possible side effects of LEMTRADA. For more information, ask your healthcare provider or pharmacist.

Call your doctor for medical advice about side effects. You may report side effects to the FDA at 1-800-FDA-1088.

General information about the safe and effective use of LEMTRADA.

This Medication Guide summarizes the most important information about LEMTRADA. If you would like more information, talk with your healthcare provider. You can ask your pharmacist or healthcare provider for information about LEMTRADA that is written for health professionals.

For more information, go to www.LemtradaREMS.com or call Genzyme at 1-855-676-6326.

What are the ingredients in LEMTRADA?

Active ingredient: alemtuzumab

Inactive ingredients: dibasic sodium phosphate, disodium edetate dihydrate, polysorbate 80, potassium chloride, potassium dihydrogen phosphate, sodium chloride, and Water for Injection, USP.

Manufactured and distributed by:
Genzyme Corporation
Cambridge, MA 02141
A SANOFI COMPANY
US License Number: 1596

LEMTRADA and CAMPATH are registered trademarks of Genzyme Corporation.
©2024 Genzyme Corporation. All rights reserved.

This Medication Guide has been approved by the U.S. Food and Drug Administration

Revised: x 2024

PRINCIPAL DISPLAY PANEL - 12 mg/1.2 mL Vial Carton

NDC 58468-0200-1

LEMTRADA®
(alemtuzumab)
injection

12 mg/1.2 mL
(10 mg/mL)

For Intravenous Infusion Only

Dilute before
Intravenous Infusion

Single-Dose Vial,
Discard Unused Portion

Rx only

Dispense the enclosed
Medication Guide to each
patient.